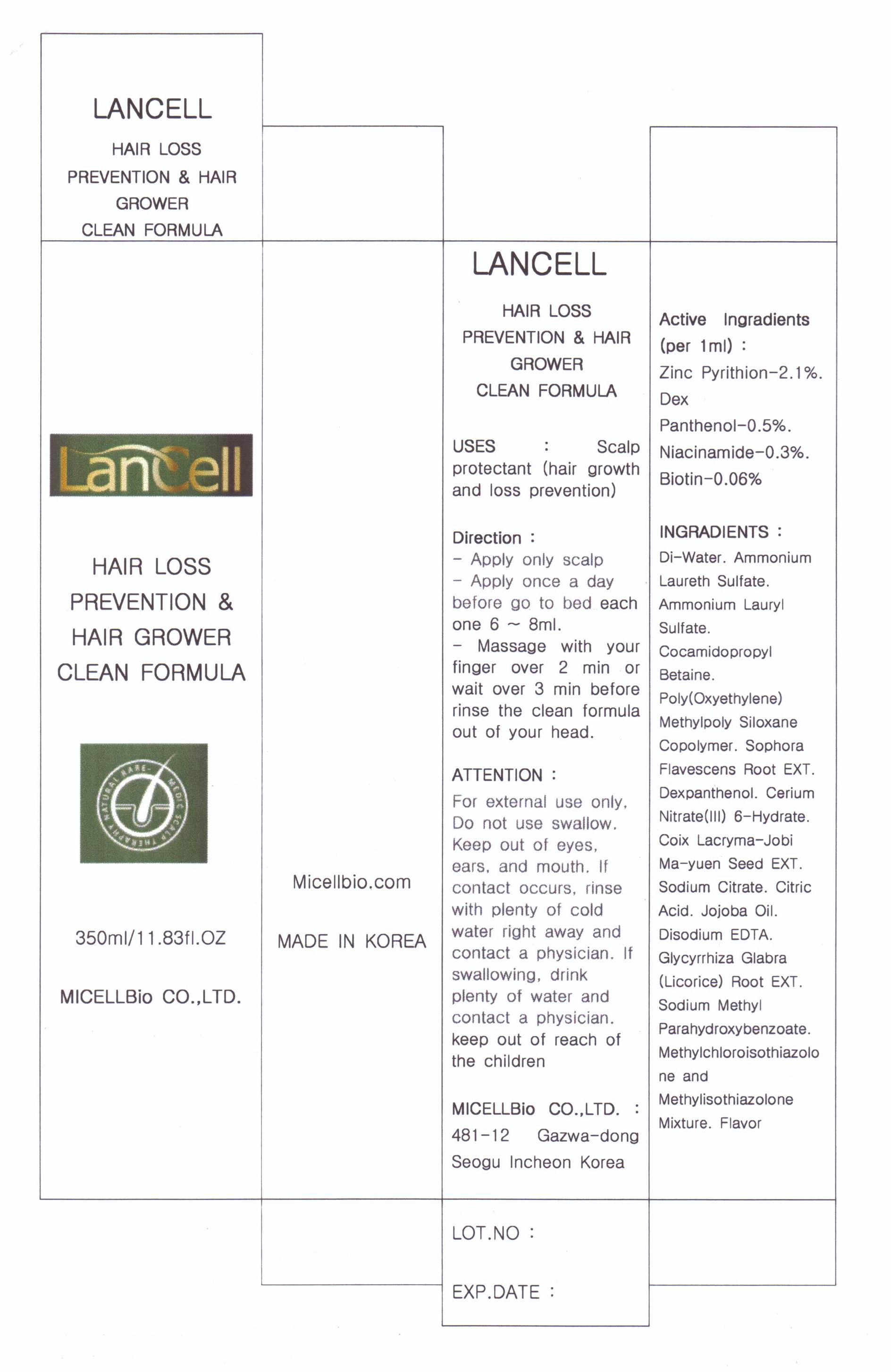 DRUG LABEL: Lancell hair loss prevention hair grower clean formula
NDC: 76084-1001 | Form: LIQUID
Manufacturer: MICELLBio Co., Ltd
Category: otc | Type: HUMAN OTC DRUG LABEL
Date: 20110407

ACTIVE INGREDIENTS: PANTHENOL 0.005 mL/1 mL; PYRITHIONE ZINC 0.021 mL/1 mL; NIACINAMIDE 0.003 mL/1 mL; BIOTIN 0.0006 mL/1 mL
INACTIVE INGREDIENTS: WATER; AMMONIUM LAURYL SULFATE; COCAMIDOPROPYL BETAINE; SOPHORA FLAVESCENS ROOT; DEXPANTHENOL; COIX LACRYMA-JOBI SEED; SODIUM CITRATE; CITRIC ACID MONOHYDRATE; JOJOBA OIL; EDETATE DISODIUM; GLYCYRRHIZA GLABRA; METHYLPARABEN SODIUM; METHYLCHLOROISOTHIAZOLINONE

Drug Facts

active ingredient: Zinc pyrithion, dex panthenol, niacinamide, biotin

inactive ingredient: di-water, ammonium laureth sulfate, ammonium lauryl sulfate, cocamidopropyl betaine, poly methylpoly siloxane copolymer, sophora flavescens root extract, dexpanthenol, cerium notrate(III) 6-hydrate, coix lacryma-jobi ma-yuen seed extract, sodium citrate, citric acid, jojoba oil, disodium edta, glycyrrhiza glaba root extract, sodium methyl parahydroxybenzoate, methylchloroisothiazolone and methylisothiazolone mixture, flavor

PURPOSE

scalp protectant (hair growth and loss prevention)

keep out of reach of the children

INDICATIONS AND USAGE

- massage with your finger more than 2 minutes and wait 3 minutes before rinsing

WARNINGS

- for external use only
- do not swallow
- keep out of eyes, ears and mouth

DOSAGE AND ADMINISTRATION

- apply only for scalp
- apply 6-8 ml once a day before go to bed